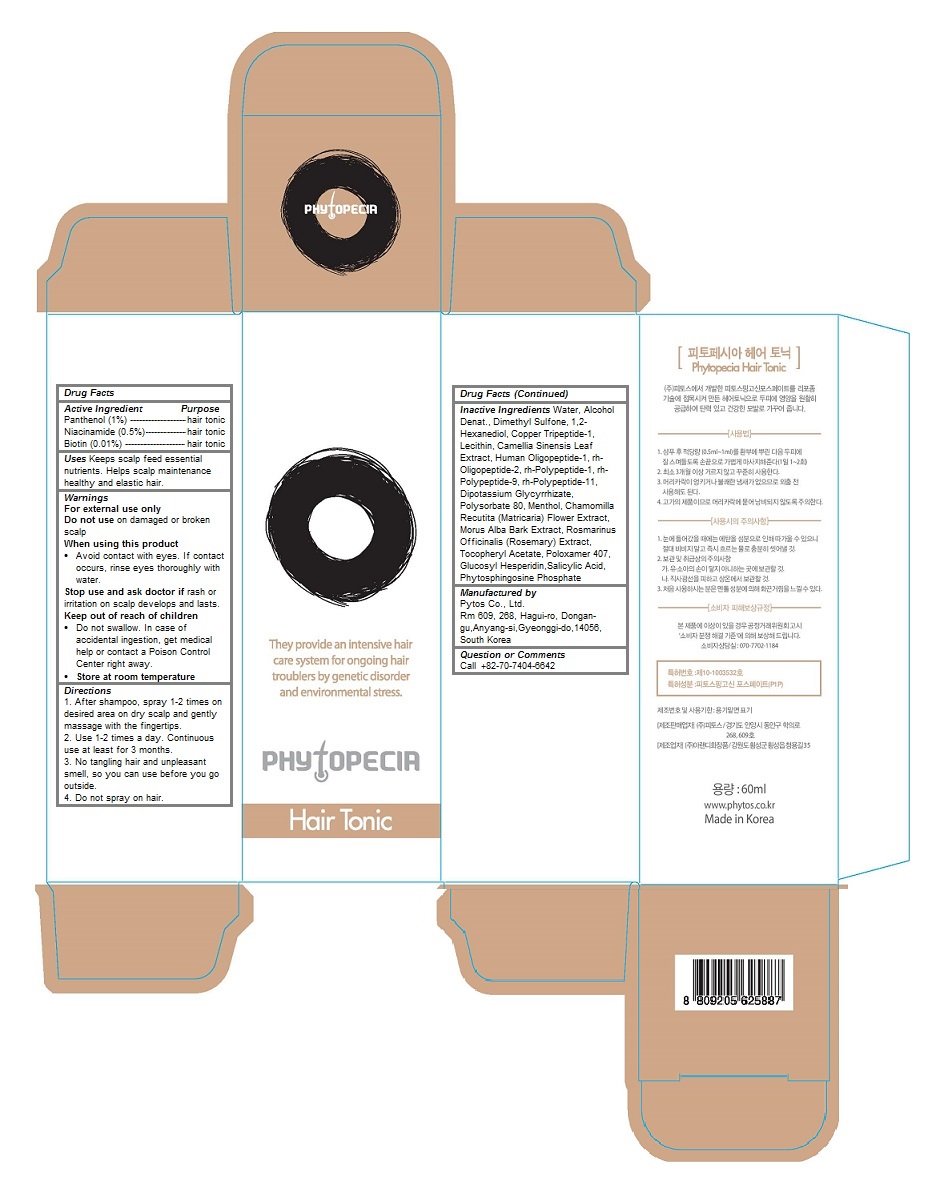 DRUG LABEL: Phytopecia Hair Tonic
NDC: 69579-106 | Form: LIQUID
Manufacturer: Phytos Co., Ltd.
Category: otc | Type: HUMAN OTC DRUG LABEL
Date: 20151218

ACTIVE INGREDIENTS: Panthenol 0.01 1/60 mL; Niacinamide 0.005 1/60 mL; biotin 0.0001 1/60 mL
INACTIVE INGREDIENTS: water; ALCOHOL; DIMETHYL SULFONE; 1,2-Hexanediol; PREZATIDE COPPER; EGG PHOSPHOLIPIDS; GREEN TEA LEAF; MECASERMIN; BASIC FIBROBLAST GROWTH FACTOR (HUMAN); FIBROBLAST GROWTH FACTOR-1; GLYCYRRHIZINATE DIPOTASSIUM; Polysorbate 80; Menthol; CHAMOMILE; MORUS ALBA BARK; ROSEMARY; .ALPHA.-TOCOPHEROL ACETATE; Poloxamer 407; Glucosyl Hesperidin; Salicylic Acid

Phytopecia Hair Tonic